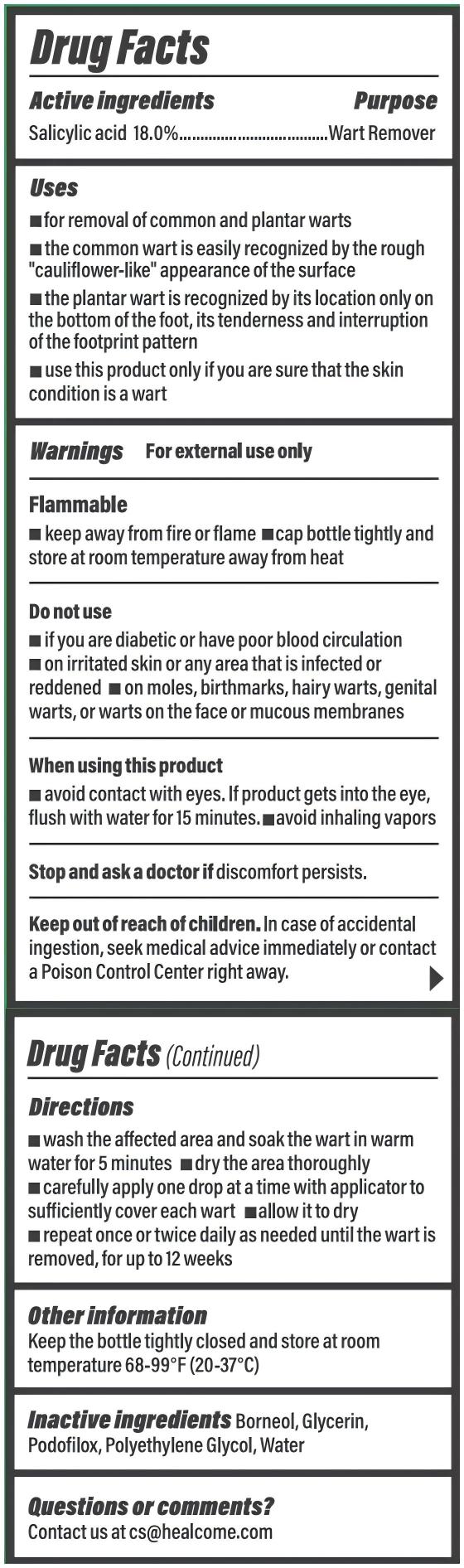 DRUG LABEL: HealCome WART REMOVER SALICYLIC ACID 18% 1.0 OZ
NDC: 83364-018 | Form: LIQUID
Manufacturer: YITONGBADA (SHENZHEN) INTERNATIONAL TRADE CO., LTD
Category: otc | Type: HUMAN OTC DRUG LABEL
Date: 20250304

ACTIVE INGREDIENTS: SALICYLIC ACID 18 g/100 mL
INACTIVE INGREDIENTS: BORNEOL; PODOFILOX; POLYETHYLENE GLYCOL, UNSPECIFIED; GLYCERIN; WATER

HealCome WART REMOVER SALICYLIC ACID 18% 1.0 OZ

HealCome WART REMOVER SALICYLIC ACID 18% 1.0 OZ

Drug Facts

Active ingredients Purpose

Salicylic acid 18.0%…............................……………………………..…..………………….Wart Remover

PURPOSE

Wart Remover

Do not use

- if you are diabetic or have poor blood circulation

- on irritated skin or any area that is infected or reddened

- on moles, birthmarks, hairy warts, genital warts, or warts on the face or mucous membranes

When using this product

- avoid contact with eyes. If product gets into the eye, flush with water for 15 minutes.

- avoid inhaling vapors

Stop and ask a doctor if discomfort persists.

Keep out of reach of children. In case of accidental ingestion, seek medical advice immediately or contact a Poison Control Center right away.

Uses

- for removal of common and plantar warts
- the common wart is easily recognized by the rough "cauliflower-like" appearance of the surface
- the plantar wart is recognized by its location only on the bottom of the foot, its tenderness and interruption of the footprint pattern
- use this product only if you are sure that the skin condition is a wart

Warnings

For external use only

------------------------------------------------------------------------------------------------------------------------------------

Flammable

- keep away from fire or flame

- cap bottle tightly and store at room temperature away from heat

Directions

- wash the affected area and soak the wart in warm water for 5 minutes

- dry the area thoroughly

- carefully apply one drop at a time with applicator to sufficiently cover each wart

- allow it to dry

- repeat once or twice daily as needed until the wart is removed, for up to 12 weeks

OTHER SAFETY INFORMATION

keep the bottle tightly closed and store at room temperature 68-99°F (20-37℃)

INACTIVE INGREDIENT

Inactive ingredients Borneol, Glycerin, Podofilox, Polyethylene Glycol, Water